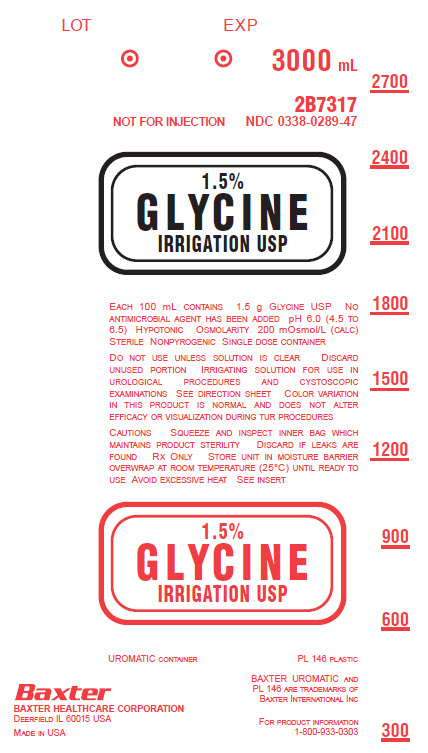 DRUG LABEL: Glycine
NDC: 0338-0289 | Form: SOLUTION
Manufacturer: Baxter Healthcare Corporation
Category: prescription | Type: HUMAN PRESCRIPTION DRUG LABEL
Date: 20180102

ACTIVE INGREDIENTS: GLYCINE 1.5 g/100 mL
INACTIVE INGREDIENTS: WATER

1.5% Glycine Irrigation, USP
in UROMATIC Plastic Container

DESCRIPTION

1.5% Glycine Irrigation, USP is a sterile, nonpyrogenic, nonhemolytic, nonelectrolytic or very weakly ionized solution in single dose UROMATIC containers for use as a urologic irrigating solution. Each liter contains 15 g Glycine, USP (NH2CH2COOH) in water for injection. pH 6.0 (4.5 to 6.5). Osmolarity 200 mOsmol/L (calc.). Normal physiologic osmolarity range is approximately 280 to 310 mOsmol/L. No antimicrobial agent has been added.

The UROMATIC plastic container is fabricated from a specially formulated polyvinyl chloride (PL 146 plastic). The amount of water that can permeate from inside the container into the overwrap is insufficient to affect the solution significantly. Solutions in contact with the plastic container can leach out certain of its chemical components in very small amounts within the expiration period, e.g., di-2-ethylhexyl phthalate (DEHP), up to 5 parts per million; however, the safety of the plastic has been confirmed in tests in animals according to USP biological tests for plastic containers as well as by tissue culture toxicity studies.

CLINICAL PHARMACOLOGY

1.5% Glycine Irrigation, USP is useful as an irrigating solution for the urinary bladder because this solution is nonhemolytic, nonelectrolytic or very weakly ionized, and provides a high degree of visibility for urologic procedures requiring endoscopy. During transurethral surgical procedures, the solution acts as a lavage for removing blood and tissue fragments. It also maintains the patency of an indwelling catheter in the immediate postoperative period.

Glycine which enters the systemic circulation is converted to serine and glyoxylic acid.

INDICATIONS AND USAGE

1.5% Glycine Irrigation, USP is indicated for use as a urologic irrigating fluid with endoscopic instruments during transurethral procedures requiring distension, irrigation, and lavage of the urinary bladder. It may be used for lavage of an indwelling catheter to maintain patency.

CONTRAINDICATIONS

Anuria.

WARNINGS

Not for injection.

Solutions for urologic irrigation must be used with caution in patients with severe cardiopulmonary or renal dysfunction.

Irrigating fluids used during transurethral prostatectomy have been demonstrated to enter the systemic circulation in relatively large volumes; thus 1.5% Glycine Irrigation, USP must be regarded as a systemic drug. Absorption of large amounts of fluids containing glycine may significantly alter cardiopulmonary and renal dynamics.

Careful cardiovascular monitoring should be maintained due to the possibility of fluid overload. Should fluid overload occur, intensive fluid and electrolyte management is necessary. Monitoring of fluid and electrolyte levels beyond the acute phase may be considered due to the possibility of delayed fluid absorption. (See ADVERSE REACTIONS, Post-Marketing Experience).

The contents of an opened container should be used promptly to minimize the possibility of bacterial growth or pyrogen formation. Discard the unused portion of irrigating solution since no antimicrobial agent has been added.

PRECAUTIONS

The cardiovascular status, especially of the patient with cardiac disease, should be carefully observed before and during transurethral resection of the prostate when using 1.5% Glycine Irrigation, USP, because the quantity of fluid absorbed into the systemic circulation by opened prostatic veins may produce significant expansion of the intravascular fluid and lead to fulminating congestive heart failure.

Shift of sodium-free intracellular fluid into the extracellular compartment, following systemic absorption, may lower serum sodium concentration and aggravate preexisting hyponatremia.

Care should be exercised if impaired liver function is known or suspected. Under such conditions ammonia resulting from metabolism of glycine may accumulate in the blood.

Pregnancy

Teratogenic Effects

Animal reproduction studies have not been conducted with 1.5% Glycine Irrigation, USP. It is not known whether 1.5% Glycine Irrigation, USP can cause fetal harm when administered to a pregnant woman or can affect reproductive capacity. 1.5% Glycine Irrigation, USP should be given to a pregnant woman only if clearly needed.

Pediatric Use

Safety and effectiveness in pediatric patients have not been established.

Geriatric Use

Clinical studies of Irrigation Solutions did not include sufficient numbers of subjects aged 65 and over to determine whether they respond differently from other younger subjects. Other reported clinical experience has not identified differences in responses between the elderly and younger patients.

Do not administer unless the solution is clear and the seal is intact.

ADVERSE REACTIONS

Adverse reactions may result from intravascular absorption of glycine. Large intravenous doses of glycine are known to cause salivation, nausea and lightheadedness. Other consequences of absorption of urologic irrigating solutions include fluid and electrolyte disturbances such as acidosis, electrolyte loss, marked diuresis, urinary retention, edema, dryness of mouth, thirst, dehydration, coma from hyponatremia, secondary hyponatremia due to fluid overload, and hyperammonemia with resultant coma and/or encephalopathy; cardiovascular disorders such as hypotension, tachycardia, angina-like pains; pulmonary disorders such as pulmonary congestion; and other general reactions such as blurred vision, convulsions, nausea, vomiting, rhinitis, chills, vertigo, backache, transient blindness and urticaria. Allergic reactions from glycine are unknown or exceedingly rare.

Should adverse reactions occur, discontinue the irrigation and re-evaluate the clinical status of the patient.

Post-Marketing Experience

Following off-label use of 1.5% Glycine Irrigation, USP for hysteroscopic procedures in women, life-threatening adverse events related to fluid overload have been reported.

OVERDOSAGE

In the event of overhydration or solute overload, re-evaluate the patient and institute appropriate corrective measures. See WARNINGS, PRECAUTIONS and ADVERSE REACTIONS.

DOSAGE AND ADMINISTRATION

The volume of solution needed will vary with the nature and duration of the urologic procedure.

If desired, warm in overwrap to near body temperature in a water bath or oven heated to not more than 45°C.

Parenteral drug products should be inspected visually for particulate matter and discoloration prior to administration whenever solution and container permit.

HOW SUPPLIED

1.5% Glycine Irrigation, USP in UROMATIC plastic containers is available as follows:

2B7317 3000mL NDC 0338-0289-47

Color variation in this product is normal and does not alter efficacy or visualization during TUR procedures.

Exposure of pharmaceutical products to heat should be minimized. Avoid excessive heat. It is recommended the product be stored at room temperature (25°C); brief exposure up to 40°C does not adversely affect the product.

Directions for Use

Tear overwrap down side at slit and remove solution container. Visually inspect the container. If the outlet port protector is damaged, detached, or not present, discard container as solution path sterility may be impaired. Some opacity of the plastic due to moisture absorption during the sterilization process may be observed. This is normal and does not affect the solution quality or safety. The opacity will diminish gradually. Check for minute leaks by squeezing bag firmly. If leaks are found, discard solution as sterility may be impaired.

Use Aseptic Technique.

1. Suspend container using hanger hole.
2. Remove protector from outlet port.
3. Attach irrigation set. Refer to complete directions accompanying set.

Baxter Healthcare Corporation
Deerfield, IL 60015 USA

Printed in USA

07-19-00-0226

Rev. January 2018

Baxter and Uromatic are trademarks of Baxter International Inc.

PACKAGE LABEL.PRINCIPAL DISPLAY PANEL

1.5% Glycine Irrigation USP Container Label

1.5% Glycine Irrigation USP Container Label

LOT

EXP

3000 mL

2B7317

NOT FOR INJECTION NDC 0338-0289-47

1.5%

GLYCINE

IRRIGATION USP

EACH 100 mL CONTAINS 1.5g GLYCINE USP NO

ANTIMICROBIAL AGENT HAS BEEN ADDED

pH 6.0 (4.5 to 6.5) HYPOTONIC OSMOLARITY 200

mOsmol/L (CALC) STERILE NONPYROGENIC SINGLE

DOSE CONTAINER

DO NOT USE UNLESS SOLUTION IS CLEAR DISCARD

UNUSED PORTION IRRIGATING SOLUTION FOR USE IN

UROLOGICAL PROCEDURES AND CYSTOSCOPIC

EXAMINATIONS SEE DIRECTION SHEET COLOR VARIATION

IN THIS PRODUCT IS NORMAL AND DOES NOT ALTER

EFFICACY OR VISUALIZATION DURING TUR PROCEDURES

CAUTIONS SQUEEZE AND INSPECT INNER BAG WHICH

MAINTAINS PRODUCT STERILITY DISCARD IF LEAKS ARE

FOUND RX ONLY STORE UNIT IN MOISTURE BARRIER

OVERWRAP AT ROOM TEMPERATURE (25°C) UNTIL READY TO

USE AVOID EXCESSIVE HEAT SEE INSERT

1.5%

GLYCINE

IRRIGATION USP

UROMATIC CONTAINER PL 146 PLASTIC

Baxter Logo

BAXTER HEALTHCARE CORPORATION

DEERFIELD IL 60015 USA

MADE IN USA

BAXTER UROMATIC AND

PL 146 ARE TRADEMARKS OF

BAXTER INTERNATIONAL INC

FOR PRODUCT INFORMATION

1-800-933-0303